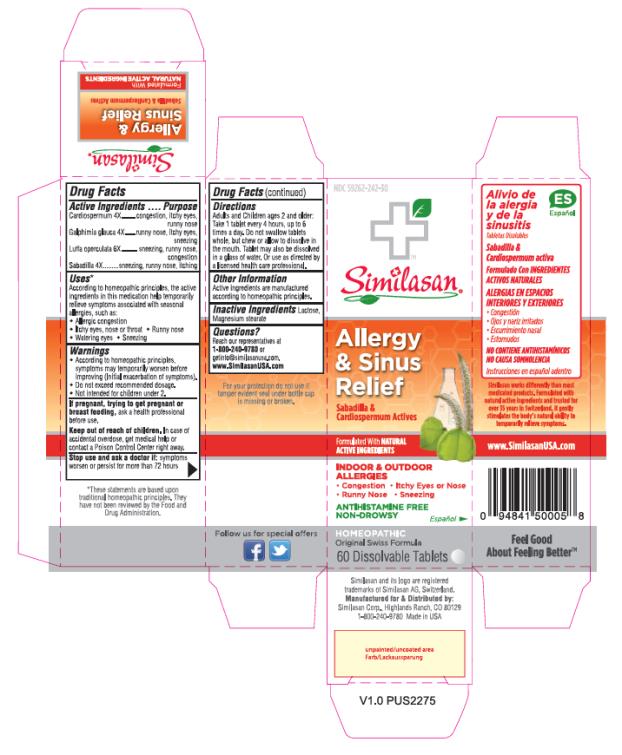 DRUG LABEL: Allergy and Sinus Relief
NDC: 59262-242 | Form: TABLET, ORALLY DISINTEGRATING
Manufacturer: Similasan Corporation
Category: homeopathic | Type: HUMAN OTC DRUG LABEL
Date: 20161212

ACTIVE INGREDIENTS: CARDIOSPERMUM HALICACABUM FLOWERING TOP 4 [hp_X]/1 1; GALPHIMIA GLAUCA FLOWERING TOP 4 [hp_X]/1 1; LUFFA OPERCULATA FRUIT 6 [hp_X]/1 1; SCHOENOCAULON OFFICINALE SEED 4 [hp_X]/1 1
INACTIVE INGREDIENTS: LACTOSE; MAGNESIUM STEARATE

Allergy and Sinus Relief

Allergy & Sinus Relief

Drug Facts

Active Ingredients

Cardiospermum 4X

Purpose

congestion, itchy eyes, runny nose

Active Ingredients

Galphimia glauca 4X

Purpose

runny nose, itchy eyes, sneezing

Active Ingredients

Luffa operculata 6X

Purpose

sneezing, runny nose, congestion

Active Ingredients

Sabadilla 4X

Purpose

sneezing, runny nose, itching

Uses*

According to homeopathic principles, the active ingredients in this medication help temporarily relieve symptoms associated with seasonal allergies, such as:

• Allergic congestion

• Itchy eyes, nose or throat

• Runny nose

• Watering eyes

• Sneezing

Warnings

• According to homeopathic principles, symptoms may temporarily worsen before improving (Initial exacerbation of symptoms).

• Do not exceed recommended dosage.

• Not intended for children under 2.

Keep out of reach of children.

In case of accidental overdose, get medical help or contact a Poison Control Center right away.

Stop use and ask a doctor if:

symptoms worsen or persist for more than 72 hours

Directions

Adults and Children ages 2 and older: Take 1 tablet every 4 hours, up to 6 times a day. Do not swallow tablets whole, but chew or allow to dissolve in the mouth. Tablet may also be dissolved in a glass of water. Or use as directed by a licensed health care professional.

Other Information

Active ingredients are manufactured according to homeopathic principles.

Inactive Ingredients

Lactose, Magnesium stearate

Questions?

Reach our representatives at 1-800-240-9780 or getinfo@similasanusa.com. www.SimilasanUSA.com

*These statements are based upon traditional homeopathic principles. They have not been reviewed by the Food and Drug Administration.

PRINCIPAL DISPLAY PANEL

NDC 59262-242-30
Similasan
Allergy
& Sinus
Relief
60 Dissolvable Tablets